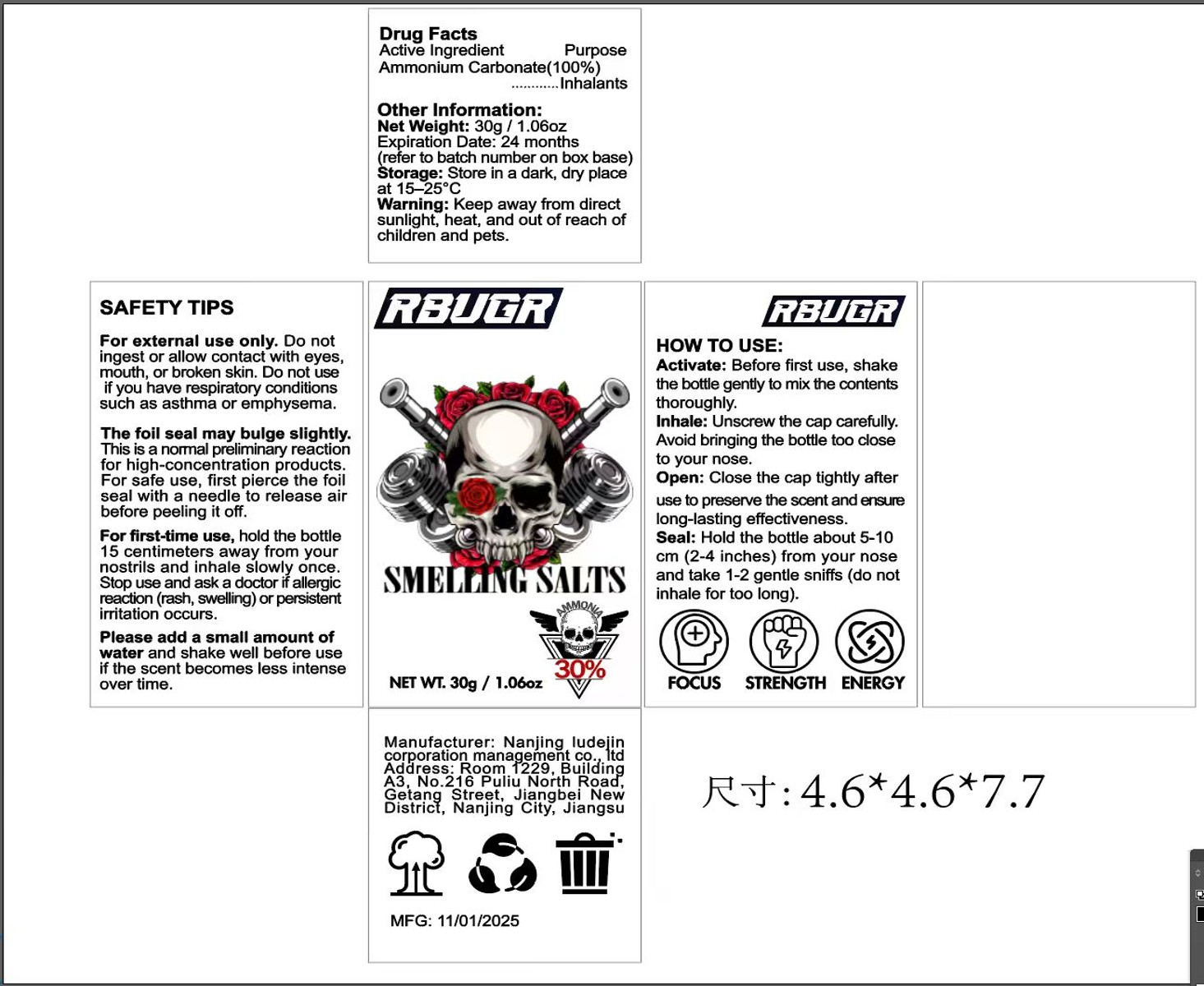 DRUG LABEL: RBUGR smelling salts
NDC: 87165-003 | Form: GRANULE
Manufacturer: Nanjing Ludejin Corporation Management Co., Ltd
Category: otc | Type: HUMAN OTC DRUG LABEL
Date: 20251106

ACTIVE INGREDIENTS: AMMONIUM CARBONATE 1 g/1 g

87165-003 RBUGR smelling salts

ACTIVE INGREDIENT

Ammonium Carbonate 100%

PURPOSE

Inhalants

INDICATIONS AND USAGE

Make people more alert and have a refreshing effect

WARNINGS

For external use only.

DO NOT USE

Do notingest or allow contact with eyesmouth, or broken skin. Do not useif you have respiratory conditionssuch as asthma or emphysema.

WHEN USING

The foil seal may bulge slightly.This is a noral preliminary reactionfor high-concentration products.For safe use, first pierce the foilseal with a needle to release airbefore peeling it off.
For first-time use, hold the bottle 15 centimeters away from yournostrils and inhale slowly once.Stop use and ask a doctor if allergicreaction (rash, swelling) or persistentirritation occurs.
Please add a small amount of water and shake well before useif the scent becomes less intenseover time.

KEEP OUT OF REACH OF CHILDREN

Keep away from directsunlight, heat, and out of reach ofchildren and pets.

DOSAGE AND ADMINISTRATION

Activate: Before first use, shakethe bottle gently to mix the contentsthoroughly.
Inhale: Unscrew the cap carefully.Avoid bringing the bottle too closeto your nose.
Open: Close the cap tightly afteruse to preserve the scent and ensurelong-lasting effectiveness
Seal: Hold the bottle about 5-10cm (2-4 inches) from your noseand take 1-2 gentle sniffs (do notinhale for too long).

INACTIVE INGREDIENT

Ammonium Carbonate 100%